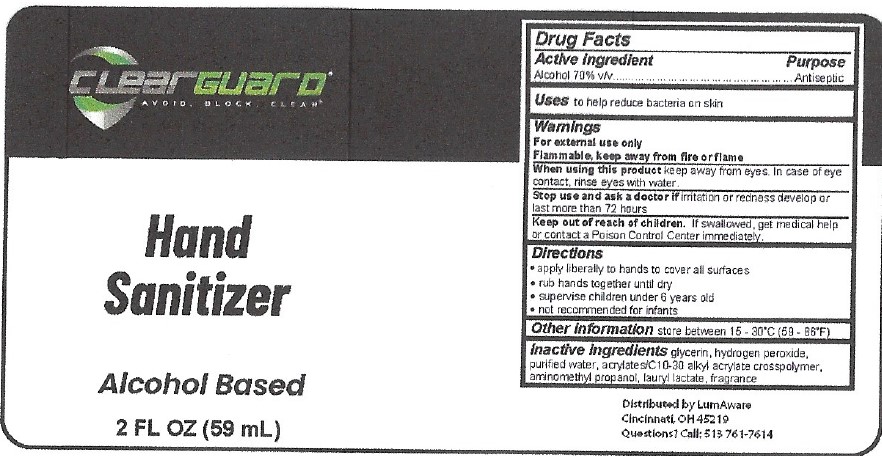 DRUG LABEL: ClearGuard Hand Sanitizer
NDC: 80996-002 | Form: SOLUTION
Manufacturer: EVP International, LLC
Category: otc | Type: HUMAN OTC DRUG LABEL
Date: 20210101

ACTIVE INGREDIENTS: ALCOHOL 70 mL/100 mL
INACTIVE INGREDIENTS: AMINOMETHYLPROPANOL; LAURYL LACTATE; HYDROGEN PEROXIDE; GLYCERIN; WATER; CARBOMER INTERPOLYMER TYPE A (55000 CPS)

ClearGuard Hand Sanitizer

Drug Facts

Active ingredient

Alcohol 70% v/v

Purpose

Antiseptic

Uses

to help reduce bacteria on skin

Warnings

For external use only

Flammable, keep away from heat or flame.

When using this product keep away from eyes. In case of eye contact, rinse eyes with water.

Stop use and ask a doctor if irritation or redness develop or last more than 72 hours.

Keep out of reach of children. If swallowed, get medial help or contact a Poison Control Center immediately.

Directions

- apply liberally to hands to cover all surfaces
- rub hands together until dry
- supervise children under 6 years old
- not recommended for infants

Other information

- store between 15-30°C (59-86°F)

Inactive ingredients

glycerin, hydrogen peroxide, purified water, acrylates/C10-30 alkyl acrylate crosspolymer, aminomethyl propanol, lauryl lactate, fragrance

Distributed by LumAware

Cincinnati, OH 45219

Questions? Call 513-761-7614

PACKAGE LABEL

ClearGuard

Hand Sanitizer

Alcohol Based

2 FL OZ (59 mL)